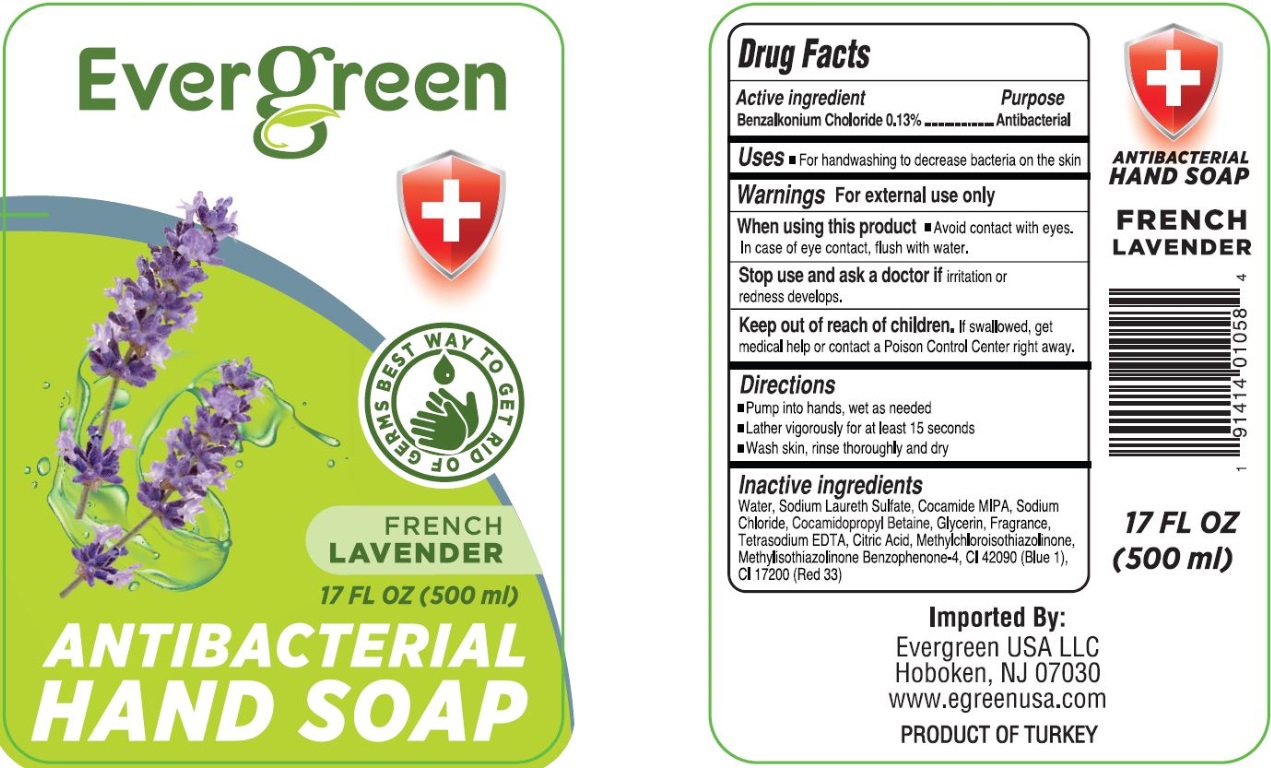 DRUG LABEL: Evergreen French Lavender Scented Antibacterial Handsoap
NDC: 74600-504 | Form: LIQUID
Manufacturer: GENC GIDA KOZMETIK VE KIMYASAL URUNLER SANAYI VE TICARET LIMITED SIRKETI
Category: otc | Type: HUMAN OTC DRUG LABEL
Date: 20200812

ACTIVE INGREDIENTS: BENZALKONIUM CHLORIDE 0.13 g/100 mL
INACTIVE INGREDIENTS: WATER; SODIUM LAURETH-3 SULFATE; COCO MONOISOPROPANOLAMIDE; SODIUM CHLORIDE; COCAMIDOPROPYL BETAINE; GLYCERIN; EDETATE SODIUM; CITRIC ACID MONOHYDRATE; METHYLCHLOROISOTHIAZOLINONE; METHYLISOTHIAZOLINONE; SULISOBENZONE; FD&C BLUE NO. 1; D&C RED NO. 33

Evergreen FRENCH LAVENDER ANTIBACTERIAL HAND SOAP

Active ingredient

Benzalkonium Chloride 0.13%

Purpose

Antibacterial

INDICATIONS AND USAGE

Uses • For handwashing to decrease bacteria on the skin

Warnings For external use only

When using this product • Avoid contact with eyes. In case of eye contact, flush with water.

Stop use and ask a doctor if irritation or redness develops.

Keep out of reach of children. If swallowed, get medical help or contact a Poison Control Center right away.

Directions

• Pump into hands, wet as needed

• Lather vigorously for at least 15 seconds

• Wash skin, rinse thoroughly and dry

Inactive ingredients

Water, Sodium Laureth Sulfate, Cocamide MIPA, Sodium Chloride, Cocamidopropyl Betaine, Glycerin, Fragrance, Tetrasodium EDTA, Citric Acid, Methylchloroisothiazolinone, Methylisothiazolinone, Benzophenone-4, CI 42090 (Blue 1), CI 17200 (Red 33)

BEST WAY TO GET RID OF GERMS

Imported By:

Evergreen USA LLC

Hoboken, NJ 07030

www.egreenusa.com

PRODUCT OF TURKEY